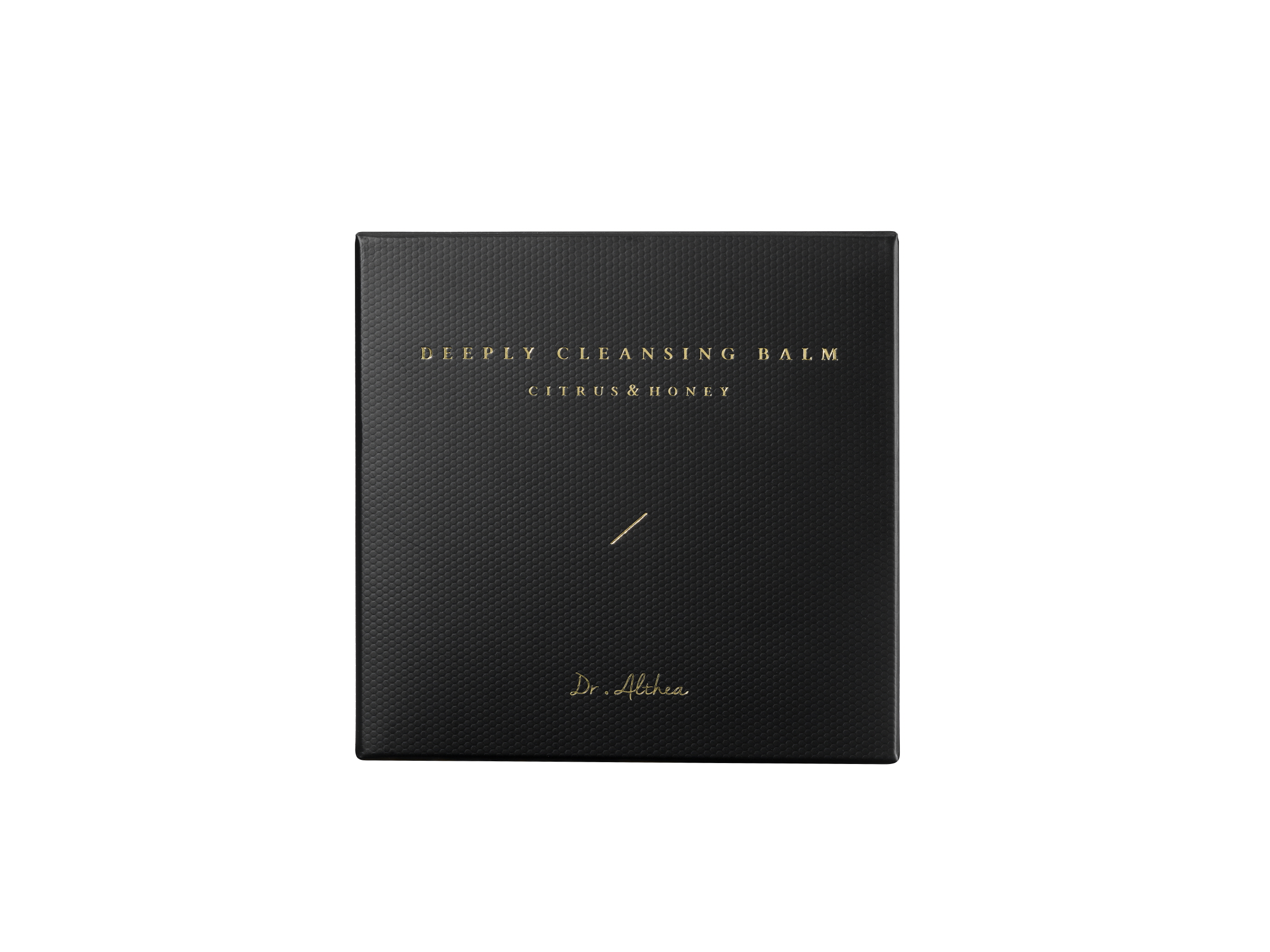 DRUG LABEL: DR.ALTHEA CITRUS AND HONEY DEEPLY CLEANSING BALM
NDC: 70905-0014 | Form: CREAM
Manufacturer: Dr. Althea
Category: otc | Type: HUMAN OTC DRUG LABEL
Date: 20170402

ACTIVE INGREDIENTS: CITRUS JUNOS FRUIT 0.01 g/100 mL; HONEY 0.01 g/100 mL
INACTIVE INGREDIENTS: MINERAL OIL; SHEA BUTTER

Drug Facts

ACTIVE INGREDIENT

CITRUS JUNOS FRUIT EXTRACT, HONEY EXTRACT

INACTIVE INGREDIENT

MINERAL OIL, ETHYLHEXYL PALMITATE, PEG-20 GLYCERYL TRIISOSTEARATE, POLYETHYLENE, 1,2-HEXANEDIOL, ELAEIS GUINEENSIS (PALM) OIL, CAMELLIA JAPONICA SEED OIL, ARGANIA SPINOSA KERNEL OIL, COCOS NUCIFERA (COCONUT) OIL, BUTYROS PERMUM PARKII (SHEA) BUTTER, SORBITAN SESQUIOLEATE, TRIHYDROXYSTEARIN, TOCOPHERYL ACETATE, FRAGRANCE

PURPOSE

Natural ingredients, such as citrus and honey, get absorbed into skin naturally to cleanse makeup residues and waste perfectly and effectively and leave lustrous skin afterwards.

keep out of reach of the children

INDICATIONS AND USAGE

1. Don’t touch water with hands, and take proper amount of it with a spoon.
2. Apply it on the whole face, and lightly massage by drawing circles.
3. After fully massaging, wipe the residue with sponge puffs.
4. Wash it with warm water and the cleanser.

WARNINGS

1 In the use of the product if the following phenomenon happen, please stop using; if continue using the situation gets worse, please consult with the doctor
1) red, itchy, tingling
2) please stop using if any of the above symptoms appear because of the sun exposure
2 Wounds, eczema, skin inflammation in the face, please do not use
3 Storage precautions
1) seale immediately after using
2) please place in theplace where the infant are unable to access in case eating by mistake
3) avoid placing in high temperature, low temperature or direct sunlight field

DOSAGE AND ADMINISTRATION

for external use only